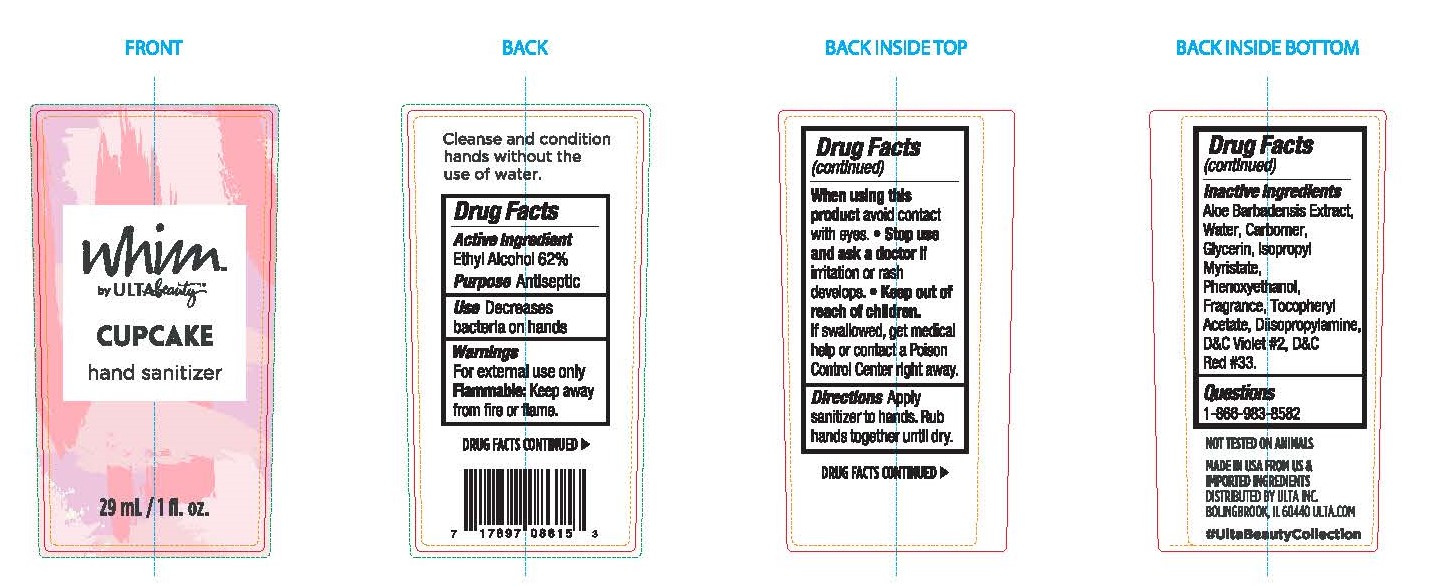 DRUG LABEL: ULTA WHIM CUPCAKE
NDC: 73708-620 | Form: GEL
Manufacturer: CarrollClean LLC
Category: otc | Type: HUMAN OTC DRUG LABEL
Date: 20200825

ACTIVE INGREDIENTS: ALCOHOL 62 mL/100 mL
INACTIVE INGREDIENTS: DIISOPROPYLAMINE 0.21 mL/100 mL; WATER 31.5 mL/100 mL; PHENOXYETHANOL 0.05 mL/100 mL; ALOE VERA LEAF 0.9 mL/100 mL; .ALPHA.-TOCOPHEROL ACETATE 0.01 mL/100 mL; CARBOMER INTERPOLYMER TYPE A (55000 CPS) 0.4 mL/100 mL; GLYCERIN 0.19 mL/100 mL; ISOPROPYL MYRISTATE 0.19 mL/100 mL

ULTA WHIM CUPCAKE

Active

Ethyl Alcohol 62%

Purpose

Antiseptic

Directions

Cleanse and condition hands without the use of water.

Use

Decreases bacteria on hands

Warnings

For external use only

Flammable: Keep away from fire or flame.

Inactive

Aloe Barbadensis Extract, Water, Carbomer, Glycerin, Isopropyl Myristate, Phenoxyethanol, Fragrance, Tocopheryl Acetate, Diisopropylamine, D&C Violet #2, D&C Red #33

Keep out of reach of children.